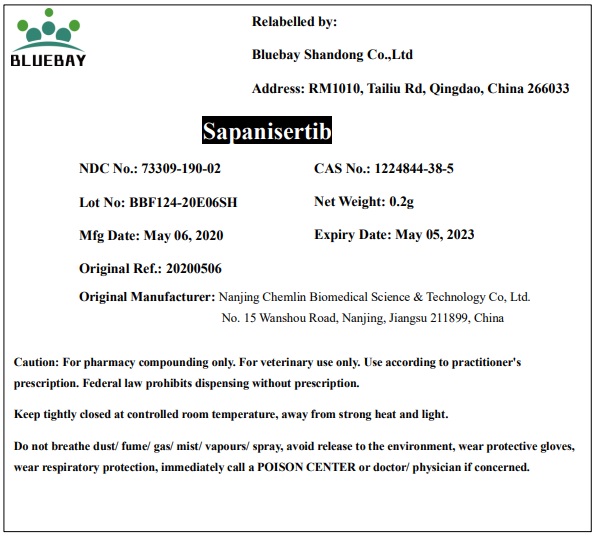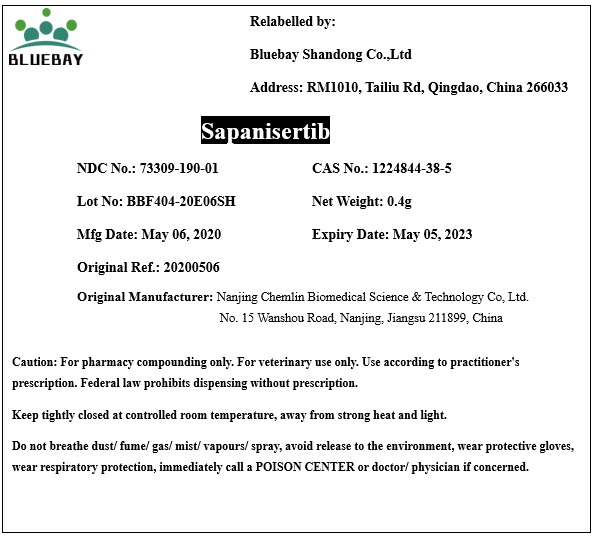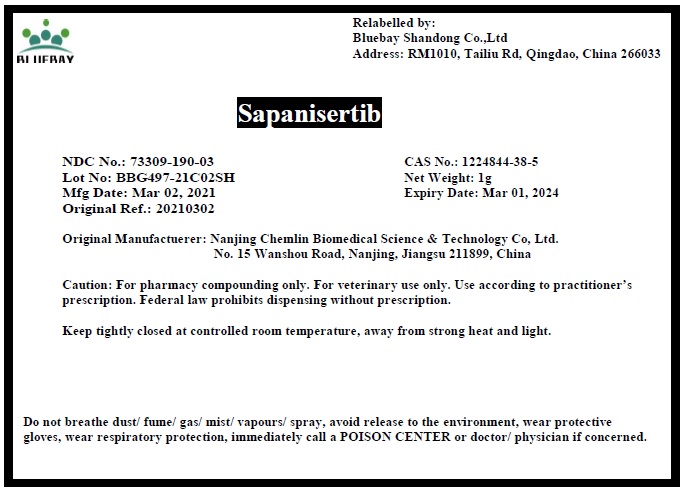 DRUG LABEL: Sapanisertib
NDC: 73309-190 | Form: POWDER
Manufacturer: BLUEBAY SHANDONG CO.,LTD
Category: other | Type: BULK INGREDIENT
Date: 20210920

ACTIVE INGREDIENTS: SAPANISERTIB 1 g/1 g

Sapanisertib